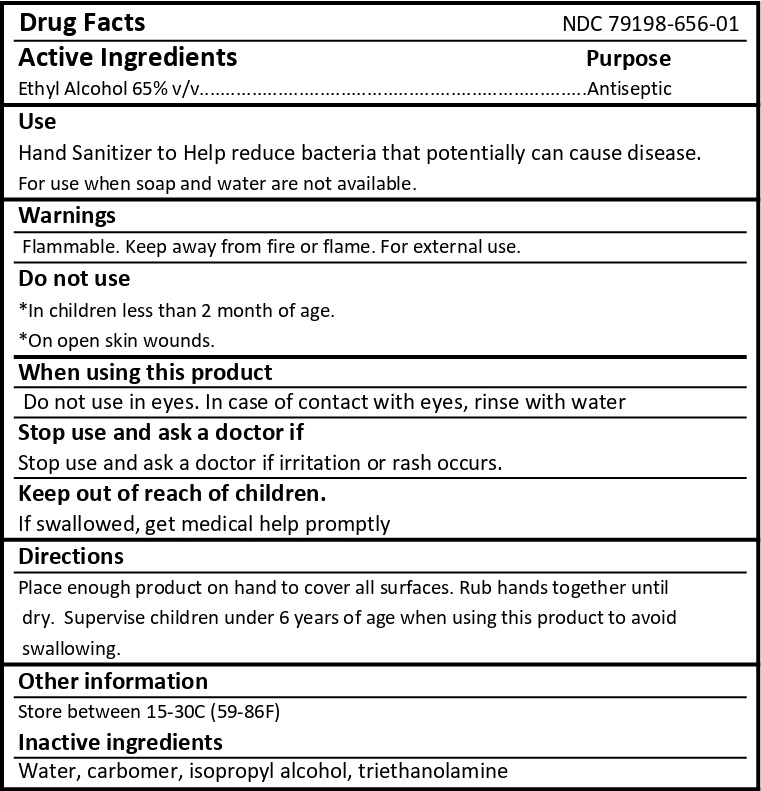 DRUG LABEL: ZEPOL
NDC: 79198-656 | Form: GEL
Manufacturer: DILE ENTERPRISES LLC
Category: otc | Type: HUMAN OTC DRUG LABEL
Date: 20200622

ACTIVE INGREDIENTS: ALCOHOL 65 mL/100 mL
INACTIVE INGREDIENTS: FENOPROP TRIETHANOLAMINE; WATER; ISOPROPYL ALCOHOL; CARBOMER 940

ACTIVE INGREDIENT

Ethyl Alcohol 65% v/v. Purpose: Antiseptic

PURPOSE

Antisptic, Hand Sanitizer

WARNINGS

Flammable. Keep awy from fire or flame. For external use.

DO NOT USE

In children less than 2 months of age

On open skin wounds

Do not use in eyes. In case of contact with eyes, rinse with water.

Stop use and ask a doctor if irritation or rash occurs.

KEEP OUT OF REACH OF CHILDREN

If swallowed, get medical help promptly.

DOSAGE AND ADMINISTRATION

Place enough product on hands to cover all surface. Rub hands together until dry.

Supervise children under 6 years of age when using this product to avoid swallowing

STORAGE AND HANDLING

Store between 15-30C (59-89F)

INDICATIONS AND USAGE

For handwashing to decrease bacteria for the skin.

INACTIVE INGREDIENT

Water, carbomer, isopropyl alcohol, triethanolamine

PACKAGE LABEL

3.785L NDC 79198-656-01